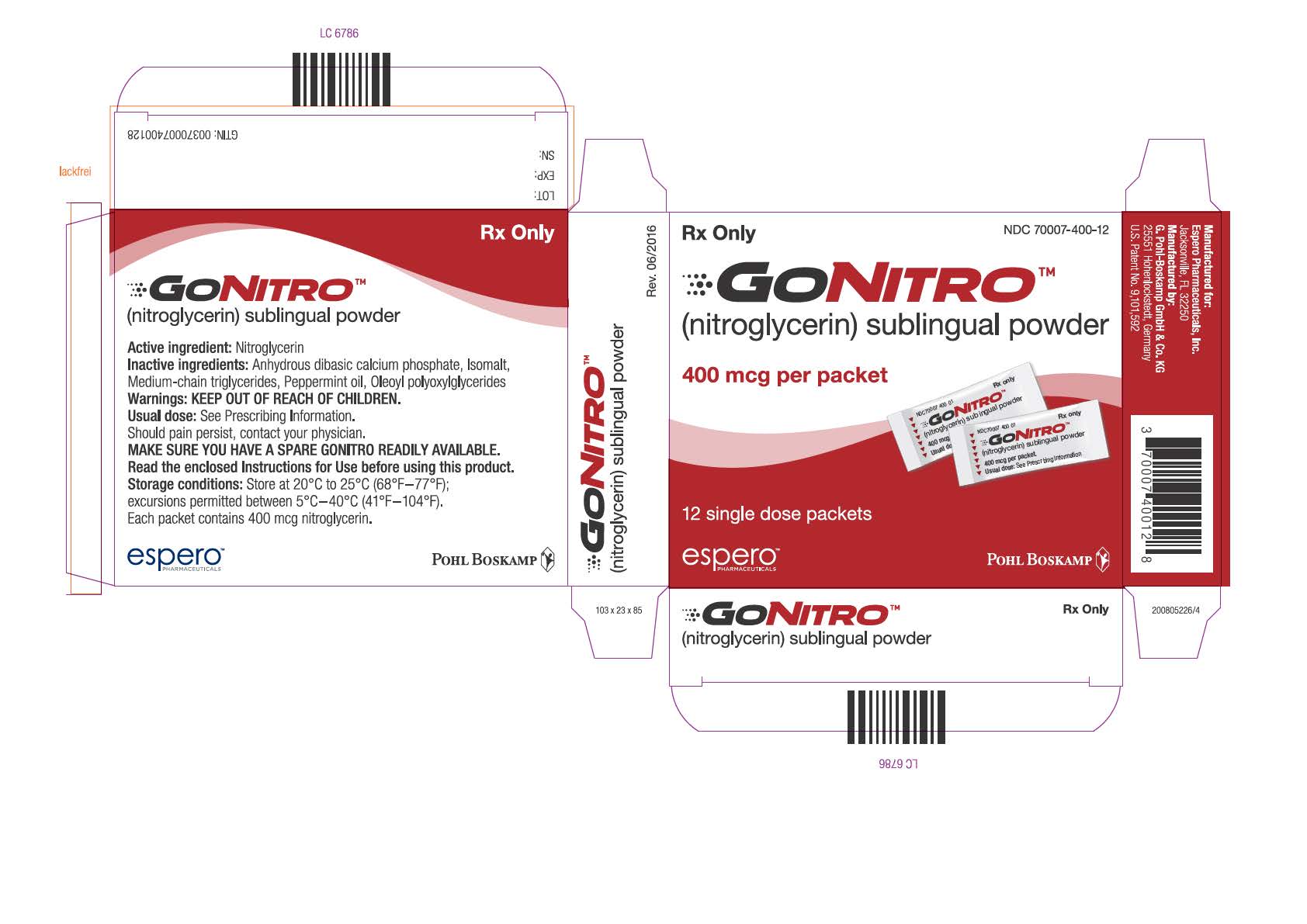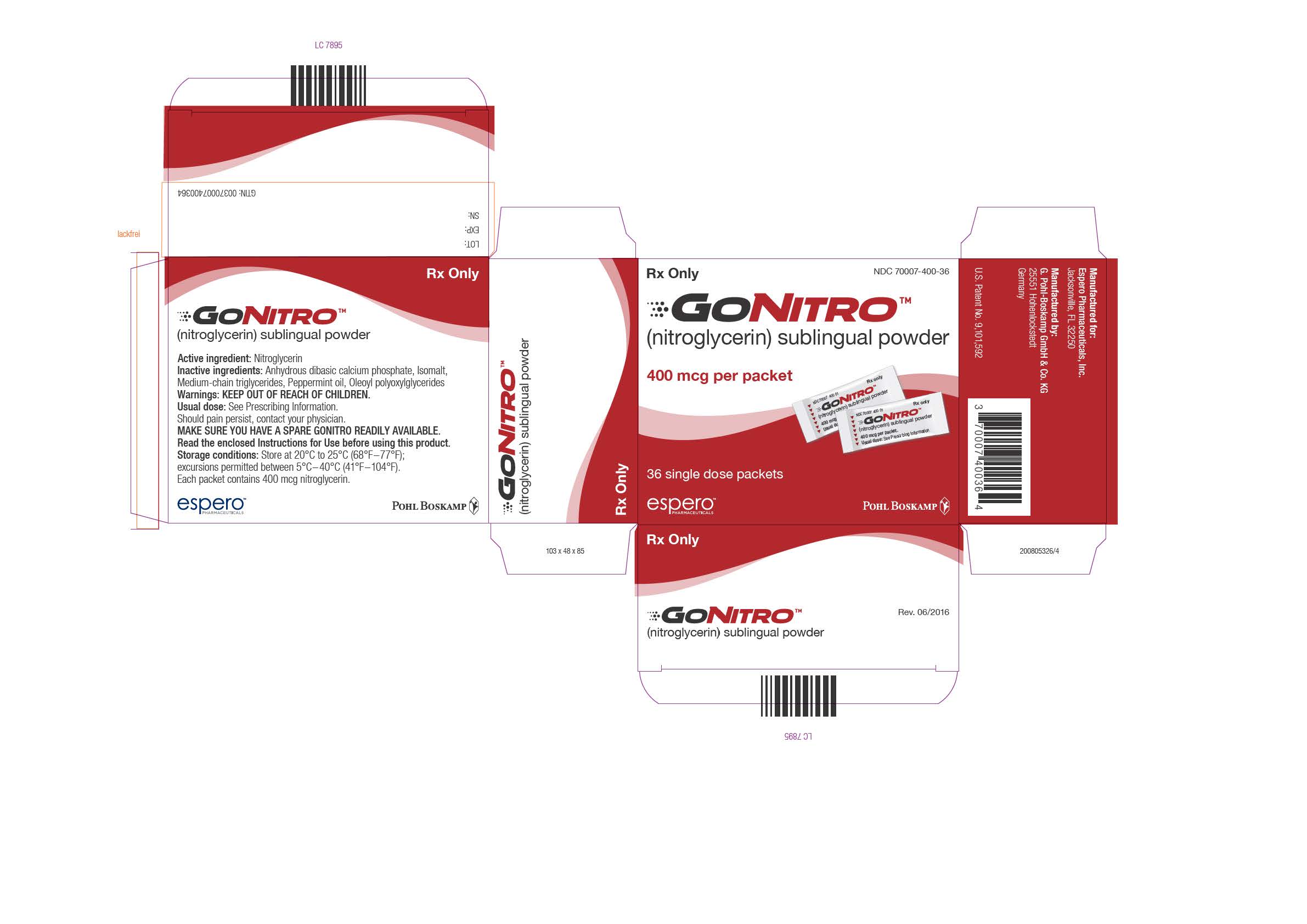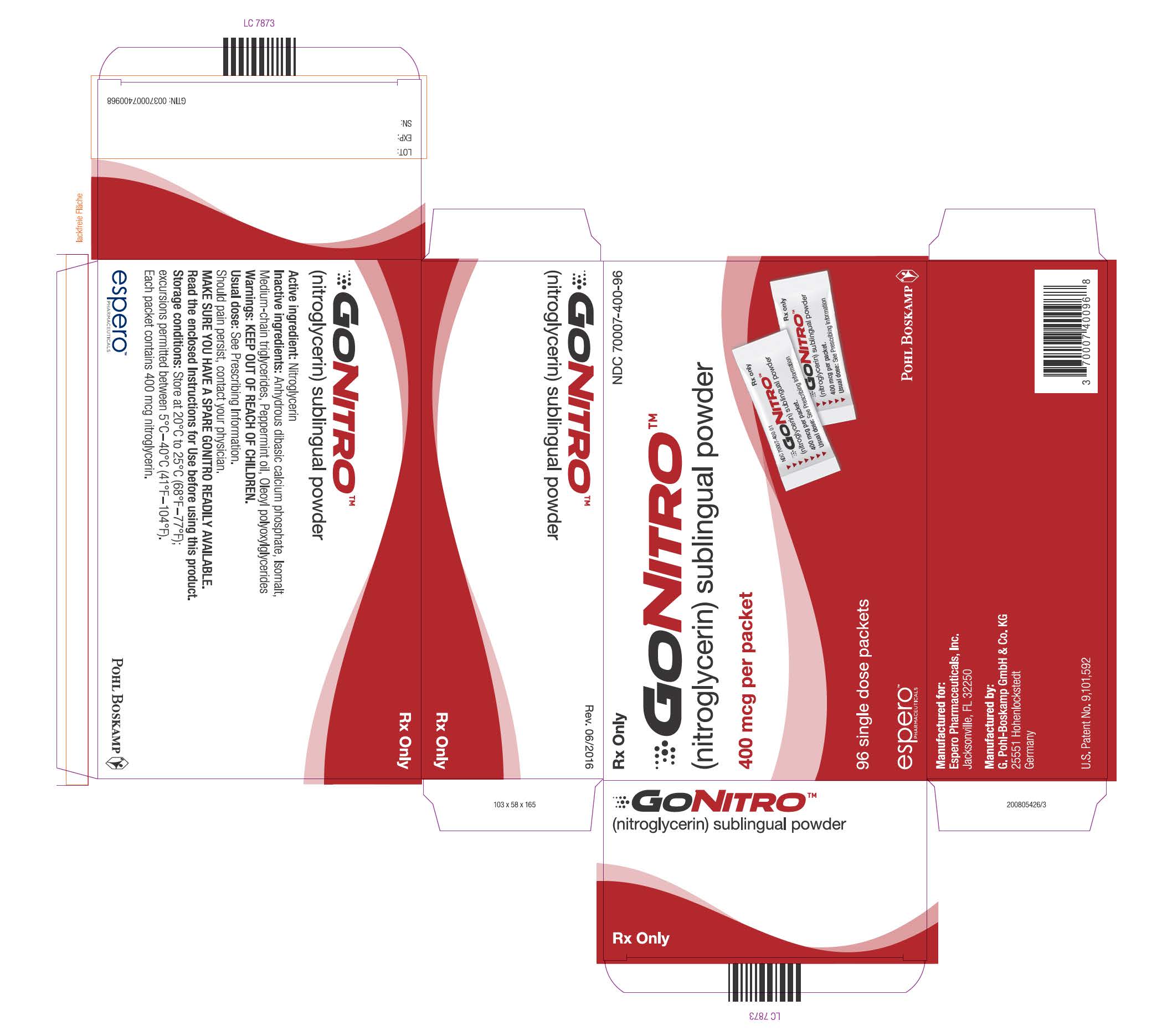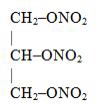 DRUG LABEL: GONITRO
NDC: 70007-400 | Form: POWDER
Manufacturer: Espero Pharmaceuticals, Inc.
Category: prescription | Type: HUMAN PRESCRIPTION DRUG LABEL
Date: 20180620

ACTIVE INGREDIENTS: NITROGLYCERIN 400 ug/1 1
INACTIVE INGREDIENTS: ANHYDROUS DIBASIC CALCIUM PHOSPHATE; ISOMALT; MEDIUM-CHAIN TRIGLYCERIDES; PEPPERMINT OIL; PEG-5 oleate

HIGHLIGHTS OF PRESCRIBING INFORMATION

These highlights do not include all the information needed to use GONITRO safely and effectively. See full prescribing information for GONITRO.
GONITRO (nitroglycerin) sublingual powder
Initial U.S. Approval:1981

1 INDICATIONS AND USAGE

GONITRO is a nitrate vasodilator indicated for acute relief of an attack or prophylaxis of angina pectoris due to coronary artery disease. (1)

2 DOSAGE AND ADMINISTRATION

- At the onset of an attack, administer one or two packets (400 mcg each) under the tongue. One additional packet may be administered every 5 minutes as needed. No more than three total packets (1200 mcg) are recommended within a 15 minute period. (2.1)
- If chest pain persists after three packets, advise prompt medical attention. (2.1)
- May be used prophylactically 5 to 10 minutes prior to engaging in activities that might precipitate an acute attack. (2.1)

3 DOSAGE FORMS AND STRENGTHS

Sublingual powder, 400 mcg per packet. (3)

4 CONTRAINDICATIONS

- Use of phosphodiesterase type 5 (PDE-5) inhibitors, such as avanafil, sildenafil, tadalafil, or vardenafil, or soluble guanylate cyclase (sGC) stimulators. (4.1, 7.1)
- Severe anemia. (4.2)
- Increased intracranial pressure. (4.3)
- Hypersensitivity to GONITRO or to other nitrates or nitrites or any excipient. (4.4)
- Circulatory failure and shock. (4.5)

5 WARNINGS AND PRECAUTIONS

- Tolerance: Excessive use may lead to tolerance. (5.1)
- Hypotension: Severe hypotension may occur. (5.2)

6 ADVERSE REACTIONS

Most common adverse reactions occurring at a frequency greater than 2% are headache, dizzinesss and paresthesia. (6)

To report SUSPECTED ADVERSE REACTIONS, contact Espero Pharmaceuticals, Inc. at 1-800-235-6520 or FDA at 1-800-FDA-1088 or www.fda.gov/medwatch.

7 DRUG INTERACTIONS

- Antihypertensives: possible additive hypotensive effects. (7.2)
- Ergotamine: increased bioavailability of ergotamine. Avoid concomitant use. (7.3)

FULL PRESCRIBING INFORMATION

1 INDICATIONS AND USAGE

GONITRO is indicated for acute relief of an attack or prophylaxis of angina pectoris due to coronary artery disease.

2 DOSAGE AND ADMINISTRATION

2.1 Recommended Dosage

Administer one or two packets (400 mcg of nitroglycerin per packet) at the onset of an attack under the tongue. One additional packet may be administered every five minutes as needed. No more than three packets are recommended within a 15-minute period. If the chest pain persists after a total of threepackets, seek prompt medical attention. GONITRO may be used prophylactically 5 to 10 minutes prior to engaging in activities that might precipitate an acute attack.

2.2 Administration

Administer GONITRO at rest, ideally in the sitting position. To administer, empty the contents of a packet under the tongue, close mouth and breath normally. Allow powder to dissolve without swallowing. Do not rinse or spit for 5 minutes after dosing.

3 DOSAGE FORMS AND STRENGTHS

GONITRO (nitroglycerin) sublingual powder, in packets containing 400 mcg of nitroglycerin.

4 CONTRAINDICATIONS

4.1 PDE-5-Inhibitors and sGC-Stimulators

Do not use GONITRO in patients who are taking PDE-5-Inhibitors, such as avanafil, sildenafil, tadalafil, or vardenafil. Concomitant use can cause severe hypotension, syncope, or myocardial ischemia [see Drug Interactions (7.1)].

Do not use GONITRO in patients who are taking soluble guanylate cyclase (sGC) stimulators, such as riociguat. Concomitant use can cause hypotension.

4.2 Severe Anemia

GONITRO is contraindicated in patients with severe anemia (large doses of nitroglycerin may cause oxidation of hemoglobin to methemoglobin and could exacerbate anemia).

4.3 Increased Intracranial Pressure

GONITRO may precipitate or aggravate increased intracranial pressure and thus should not be used in patients with possible increased intracranial pressure (e. g. cerebral hemorrhage or traumatic brain injury).

4.4 Hypersensitivity

GONITRO is contraindicated in patients who are allergic to nitroglycerin, other nitrates or nitrites or any excipient.

4.5 Circulatory Failure and Shock

GONITRO is contraindicated in patients with acute circulatory failure or shock.

5 WARNINGS AND PRECAUTIONS

5.1 Tolerance

Excessive use may lead to the development of tolerance. Only the smallest number of doses required for effective relief of the acute angina attack should be used [see Dosage and Administration (2.1)].

5.2 Hypotension

Severe hypotension, particularly with upright posture, may occur even with small doses of nitroglycerin particularly in patients with constrictive pericarditis, aortic or mitral stenosis, patients who may be volume-depleted, or are already hypotensive. Hypotension induced by nitroglycerin may be accompanied by paradoxical bradycardia and increased angina pectoris. Symptoms of severe hypotension (nausea, vomiting, weakness, pallor, perspiration and collapse/syncope) may occur even with therapeutic doses.

5.3 Hypertrophic Obstructive Cardiomyopathy

Nitrate therapy may aggravate the angina caused by hypertrophic obstructive cardiomyopathy.

5.4 Headache

Nitroglycerin produces dose-related headaches, especially at the start of nitroglycerin therapy, which may be severe and persistent but usually subside with continued use.

6 ADVERSE REACTIONS

6.1 Clinical Trials Experience

Because clinical trials are conducted under widely varying conditions, adverse reaction rates observed in the clinical trials of a drug cannot be directly compared to rates in the clinical trials of another drug and may not reflect the rates observed in clinical practice.

Adverse reactions occurring at a frequency greater than 2% and greater than placebo included: headache, dizziness, and paresthesia.

6.2 Postmarketing Experience

The following adverse reactions have been identified during post-approval use of GONITRO and other nitroglycerin drugs. Because these reactions are reported voluntarily from a population of uncertain size, it is not always possible to estimate their frequency reliably or establish a causal relationship to drug exposure.

Neurologic: weakness, drowsiness
Dermatologic: cutaneous vasodilation, flushing, drug rash, exfoliative dermatitits
Gastrointestinal: nausea, vomiting
Respiratory: transient hypoxemia
Cardiovascular: tachycardia

7 DRUG INTERACTIONS

7.1 PDE-5-Inhibitors and sGC-Stimulators

GONITRO is contraindicated in patients who are using a selective inhibitor of cyclic guanosine monophosphate (cGMP)-specific phosphodiesterase type 5 (PDE-5). PDE-5-Inhibitors such as avanafil, sildenafil, vardenafil, and tadalafil have been shown to potentiate the hypotensive effects of organic nitrates.

GONITRO is contraindicated in patients who are taking soluble guanylate cyclase (sGC) stimulators. Concomitant use can cause hypotension.

The time course and dose dependence of these interactions have not been studied, and use within a few days of one another is not recommended. Appropriate supportive care for the severe hypotension has not been studied, but it seems reasonable to treat this as a nitrate overdose, with elevation of the extremities and with central volume expansion.

7.2 Antihypertensives

Patients receiving antihypertensive drugs, beta-adrenergic blockers, and nitrates should be observed for possible additive hypotensive effects. Marked orthostatic hypotension has been reported when calcium channel blockers and organic nitrates were used concomitantly.

Beta-adrenergic blockers blunt the reflex tachycardia produced by nitroglycerin without preventing its hypotensive effects. If beta-blockers are used with nitroglycerin in patients with angina pectoris, additional hypotensive effects may occur.

7.3 Ergotamine

Oral administration of nitroglycerin markedly decreases the first-pass metabolism of dihydroergotamine and subsequently increases its oral bioavailability. Ergotamine is known to precipitate angina pectoris. Therefore, patients receiving sublingual nitroglycerin should avoid ergotamine and related drugs or be monitored for symptoms of ergotism if this is not possible.

8 USE IN SPECIFIC POPULATIONS

8.1 Pregnancy

Risk summary

Limited published data on the use of nitroglycerin are insufficient to determine a drug associated risk of major birth defects or miscarriage. In animal reproduction studies, there were no adverse developmental effects when nitroglycerin was administered intravenously to rabbits or intraperitoneally to rats during organogenesis at doses greater than 64-times the human dose [see Data].

The estimated background risk of major birth defects and miscarriage for the indicated population is unknown. In the U.S. general population, the estimated background risk of major birth defects and miscarriage in clinically recognized pregnancies is 2-4% and 15-20%, respectively.

Data

Animal Data

No embryotoxic or postnatal development effects were observed with transdermal application in pregnant rabbits and rats at doses up to 240 mg/kg/day for 13 days, at intraperitoneal doses in pregnant rats up to 20 mg/kg/day for 11 days, and at intravenous doses in pregnant rabbits up to 4 mg/kg/day for 13 days.

8.2 Lactation

Risk summary

Sublingual nitroglycerin has not been studied in lactating women. It is not known if nitroglycerin is present in human milk or if nitroglycerin has effects on milk production. The developmental and health benefits of breastfeeding should be considered along with the mother’s clinical need for nitroglycerin and any potential adverse effects on the breastfed child from nitroglycerin or from the underlying maternal condition.

8.4 Pediatric Use

Safety and effectiveness of nitroglycerin in pediatric patients have not been established.

8.5 Geriatric Use

Clinical studies did not include sufficient numbers of subjects aged 65 and over to determine whether they respond differently from younger subjects. Other reported clinical experience has not identified differences in responses between elderly (greater than or equal to 65 years) and younger (less than 65 years) patients. In general, dose selection for an elderly patient should start at the low end of the dosing range, reflecting the greater frequency of decreased hepatic, renal, or cardiac function, and of concomitant disease or other drug therapy.

10 OVERDOSAGE

10.1 Signs and Symptoms, Methemoglobinemia

Nitrate overdosage may result in: severe hypotension, persistent throbbing headache, vertigo, palpitation, visual disturbance, flushing and perspiring skin (later becoming cold and cyanotic), nausea and vomiting (possibly with colic and even bloody diarrhea), syncope (especially in the upright posture), methemoglobinemia with cyanosis and anorexia, initial hyperpnea, dyspnea and slow breathing, slow pulse (dicrotic and intermittent), heart block, increased intracranial pressure with cerebral symptoms of confusion and moderate fever, paralysis and coma followed by clonic convulsions, and possibly death due to circulatory collapse.

Case reports of clinically significant methemoglobinemia are rare at conventional doses of organic nitrates. The formation of methemoglobin is dose-related and in the case of genetic abnormalities of hemoglobin that favor methemoglobin formation, even conventional doses of organic nitrates could produce harmful concentrations of methemoglobin.

10.2 Treatment of Overdosage

As hypotension associated with nitroglycerin overdose is the result of venodilatation and arterial hypovolemia, prudent therapy in this situation should be directed toward increase in central fluid volume. No specific antagonist to the vasodilator effects of nitroglycerin is known. Keep the patient recumbent in a shock position and comfortably warm. Passive movement of the extremities may aid venous return. Intravenous infusion of normal saline or similar fluid may also be necessary. Administer oxygen and artificial ventilation, if necessary. If methemoglobinemia is present, administration of methylene blue (1% solution), 1-2 mg per kilogram of body weight intravenously, may be required unless the patient is known to have G-6-PD deficiency. If an excessive quantity of GONITRO has been recently swallowed gastric lavage may be of use.

As epinephrine is ineffective in reversing the severe hypotensive events associated with overdosage, it is not recommended for resuscitation.

11 DESCRIPTION

Nitroglycerin, an organic nitrate, is a vasodilator which has effects on both arteries and veins. The chemical name for nitroglycerin is 1,2,3-propanetriol trinitrate (C3H5N3O9). The compound has a molecular weight of 227.09. The chemical structure is:

GONITRO is a powder containing nitroglycerin. Each packet of GONITRO delivers 400 mcg of nitroglycerin when administered under the tongue. The sublingual powder is formulated with the following inactive ingredients: anhydrous dibasic calcium phosphate, isomalt, medium-chain triglycerides, peppermint oil, and oleoyl polyoxylglycerides.

12 CLINICAL PHARMACOLOGY

12.1 Mechanism of Action

Nitroglycerin forms free radical nitric oxide (NO), which activates guanylate cyclase, resulting in an increase of guanosine 3',5'-monophosphate (cyclic GMP) in smooth muscle and other tissues. This eventually leads to dephosphorylation of myosin light chains, which regulates the contractile state in smooth muscle and results in vasodilatation.

12.2 Pharmacodynamics

The principal pharmacological action of nitroglycerin is relaxation of vascular smooth muscle. Although venous effects predominate, nitroglycerin produces, in a dose-related manner, dilation of both arterial and venous beds. Dilation of the postcapillary vessels, including large veins, promotes peripheral pooling of blood, decreases venous return to the heart, and reduces left ventricular end-diastolic pressure (preload). Nitroglycerin also produces arteriolar relaxation, thereby reducing peripheral vascular resistance and arterial pressure (after load), and dilates large epicardial coronary arteries; however, the extent to which this latter effect contributes to the relief of exertional angina is unclear.

Therapeutic doses of nitroglycerin may reduce systolic, diastolic and mean arterial blood pressure. Effective coronary perfusion pressure is usually maintained, but can be compromised if blood pressure falls excessively or increased heart rate decreases diastolic filling time.

Elevated central venous and pulmonary capillary wedge pressures, and pulmonary and systemic vascular resistance are also reduced by nitroglycerin therapy. Heart rate is usually slightly increased, presumably a reflex response to the fall in blood pressure. Cardiac index may be increased, decreased, or unchanged. Myocardial oxygen consumption or demand (as measured by the pressure-rate product, tension-time index, and stroke-work index) is decreased and a more favorable supply-demand ratio can be achieved. Patients with elevated left ventricular filling pressure and increased systemic vascular resistance in association with a depressed cardiac index are likely to experience an improvement in cardiac index. In contrast, when filling pressures and cardiac index are normal, cardiac index may be slightly reduced following nitroglycerin administration.

12.3 Pharmacokinetics

In a pharmacokinetic study a single 800 mcg dose of GONITRO was administered sublingually to healthy volunteers (n = 32), the mean Cmax and tmax for GTN were 1,700 pg/mL and 7 minutes, respectively. Additionally, in these subjects the mean area under the curve (AUC) for GTN was 12,300 pg/mL . min.

The results of the study indicate that the sublingual absorption of GTN is higher following the administration of GONITRO compared to Nitrolingual® Pumpspray.

A liver reductase enzyme is of primary importance in the metabolism of nitroglycerin to glycerol di- and mononitrate metabolites and ultimately to glycerol and organic nitrate. Known sites of extrahepatic metabolism include red blood cells and vascular walls. In addition to nitroglycerin, 2 major metabolites, 1,2- and 1,3-dinitroglycerin are found in plasma. The mean elimination half-life of both 1,2- and 1,3-dinitroglycerin is about 40 minutes. The 1,2- and 1,3-dinitroglycerin metabolites have been reported to possess some pharmacological activity, whereas the glycerol mononitrate metabolites of nitroglycerin are essentially inactive. Higher plasma concentrations of the dinitro metabolites, with their nearly 8-fold longer elimination half-lives, may contribute significantly to the duration of pharmacologic effect.

The volume of distribution of nitroglycerin following intravenous administration is 3.3 L/kg.

Drug interactions

Aspirin: Coadministration of nitroglycerin with high dose aspirin (1000 mg) results in increased exposure to nitroglycerin. The vasodilatory and hemodynamic effects of nitroglycerin may be enhanced by concomitant administration of nitroglycerin with high dose aspirin.

Tissue-type plasminogen activator (t-PA): Concomitant administration of t-PA and intravenous nitroglycerin has been shown to reduce plasma levels of t-PA and its thrombolytic effect.

13 NONCLINICAL TOXICOLOGY

13.1 Carcinogenesis, Mutagenesis, Impairment of Fertility

Animal carcinogenesis studies with sublingual nitroglycerin have not been performed.

Rats receiving up to 434 mg/kg/day of dietary nitroglycerin for 2 years developed dose-related fibrotic and neoplastic changes in liver, including carcinomas, and interstitial cell tumors in testes. At high dose, the incidences of hepatocellular carcinomas in both sexes were 52 % vs. 0 % in controls, and incidences of testicular tumors were 52 % vs. 8 % in controls. Lifetime dietary administration of up to 1058 mg/kg/day of nitroglycerin was not tumorigenic in mice.

Nitroglycerin was weakly mutagenic in Ames tests performed in two different laboratories. There was no evidence of mutagenicity in an in vivo dominant lethal assay with male rats treated with doses up to about 363 mg/kg/day, p.o., or in in vitro cytogenic tests in rat and dog tissues and for chromosomal aberration in Chinese hamster ovary cells.

In a three-generation reproduction study, rats received dietary nitroglycerin at doses up to about 434 mg/kg/day for six months prior to mating of the F0 generation with treatment continuing through successive F1 and F2 generations. The high dose was associated with decreased feed intake and body weight gain in both sexes at all matings. No specific effect on the fertility of the F0 generation was seen. Infertility noted in subsequent generations, however, was attributed to increased interstitial cell tissue and aspermatogenesis in the high-dose males. In this three-generation study there was no clear evidence of teratogenicity.

14 CLINICAL STUDIES

In a randomized, double-blind single-dose, 5-period cross-over study in 51 patients with exertional angina pectoris significant dose-related increases in exercise tolerance, time to onset of angina and ST-segment depression were seen following doses of 200-1600 mcg of sublingual nitroglycerin as compared to placebo.

The drug showed a profile of mild to moderate adverse events.

16 HOW SUPPLIED/STORAGE AND HANDLING

Each box of GONITRO (nitroglycerin) sublingual powder, contains 12, 36 or 96 packets.

Each packet contains 400 mcg of nitroglycerin.

GONITRO is available as:
• Box of 12 packets NDC 70007-400-12
• Box of 36 packets NDC 70007-400-36
• Box of 96 packets NDC 70007-400-96

Store at 20°C - 25°C (68°F - 77°F); excursions permitted between 5°C – 40°C (41°F – 104°F).

Rx Only.

17 PATIENT COUNSELING INFORMATION

Advise the patient to read the FDA-approved Instructions for Use.

Manufactured for
Espero Pharmaceuticals, Inc.
Jacksonville, FL 32250
(800) 235-6520
by G. Pohl-Boskamp GmbH & Co. KG
25551 Hohenlockstedt, Germany.

U.S. Patent No. 9,101,592

PATIENT INFORMATION

Instructions for Use
GONITRO (GO-NYE-troh)
(nitroglycerin)
sublingual powder

Read these Instructions for Use before you start taking GONITRO and each time you get a refill. There may be new information. This information does not take the place of talking to your healthcare provider about your medical condition or your treatment.

Important information:

- GONITROis for use under the tongue.
- A dose of GONITROmay be either 1 or 2 packets. Follow your healthcare provider’s instructions about how many packets you should take for each dose. After you take your first dose of GONITRO, you may take 1 additional packet of GONITROevery 5 minutes, if needed.
- You should not take more than 3 packets of GONITRO within 15 minutes.
- Get emergency medical help right away if you still have chest pain after taking a total of 3 packets of GONITRO.
- It is best to take GONITROwhile you are resting and in a sitting position.

Taking a dose of GONITRO
Step 1. Hold the packet of GONITROupright with the notch and red arrow line at the top of the packet.
Step 2. Tap the bottom of the GONITRO packet so that the powder settles at the bottom of the packet.
Step 3. Hold the GONITROpacket at the notch. Hold the packet as close to your mouth as possibleand tear along the red arrow line.
Step 4. Lift up your tongue.
Step 5. Pour all of the powder in the GONITRO packet under your tongue.
Step 6. Close your mouth right away and breathe normally through your nose. Allow all of the powder to dissolve before you swallow. Do not rinse your mouth or spit for 5 minutes after taking GONITRO.
Step 7. If another dose of GONITROis needed, repeat Steps 1 through 6.

- Regularly check the number of packets remaining in your GONITRO box and refill your prescription when there are three packets remaining.

How should I store GONITRO

Store GONITROat room temperature between 68°F to 77°F (20°C to 25°C).

Keep GONITROand all medicines out of the reach of children.

These Instructions for Use have been approved by the U.S. Food and Drug Administration.

Manufactured for
Espero Pharmaceuticals, Inc.
Jacksonville, FL 32250
(800) 235-6520
by G. Pohl-Boskamp GmbH & Co. KG
25551 Hohenlockstedt, Germany.

Issued: 06/2016

PACKAGE LABEL

Prinicpal Display Panel
NDC 70007-400-12
GONITRO™
(nitroglycerin)
sublingual powder
400 mcg per packet
12 single dose packets

Prinicpal Display Panel
NDC 70007-400-36
GONITRO™
(nitroglycerin)
sublingual powder
400 mcg per packet
36 single dose packets

Prinicpal Display Panel
NDC 70007-400-96
GONITRO™
(nitroglycerin)
sublingual powder
400 mcg per packet
96 single dose packets